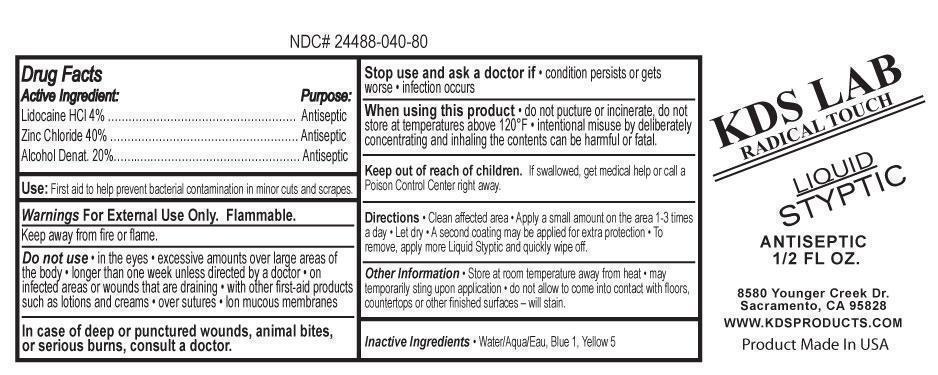 DRUG LABEL: KDS Lab
NDC: 24488-040 | Form: LIQUID
Manufacturer: KDS Lab
Category: otc | Type: HUMAN OTC DRUG LABEL
Date: 20121003

ACTIVE INGREDIENTS: LIDOCAINE HYDROCHLORIDE 39.9680796 mg/1 mL; ZINC CHLORIDE 400.018936 mg/1 mL; ALCOHOL 199.975654 mg/1 mL
INACTIVE INGREDIENTS: WATER; FD&C BLUE NO. 1; FD&C YELLOW NO. 5

Active Ingredient:

Lidocaine HCl 4% ………………………………………………
Zinc Chloride 40% ………………………………………………
Alcohol Denat. 20%……..….……………………………………

Purpose:

Antiseptic
Antiseptic
Antiseptic

Use:

First aid to help prevent bacterial contamination in minor cuts and scrapes.

Warnings

For External Use Only. Flammable.
Keep away from fire or flame.

Do not use

• in the eyes • excessive amounts over large areas of
the body • longer than one week unless directed by a doctor • on
infected areas or wounds that are draining • with other first-aid products
such as lotions and creams • over sutures • lon mucous membranes

In case of deep or punctured wounds, animal bites, or serious burns, consult a doctor.

Stop use and ask a doctor if

• condition persists or gets
worse • infection occurs

When using this product

• do not pucture or incinerate, do not
store at temperatures above 120°F • intentional misuse by deliberately
concentrating and inhaling the contents can be harmful or fatal.

Keep out of reach of children.

f swallowed, get medical help or call a
Poison Control Center right away.

Directions

Clean affected area • Apply a small amount on the area 1-3 times
a day • Let dry • A second coating may be applied for extra protection • To
remove, apply more Liquid Styptic and quickly wipe off.

Other Information

• Store at room temperature away from heat • may
temporarily sting upon application • do not allow to come into contact with floors,
countertops or other finished surfaces – will stain.

Inactive Ingredients

• Water/Aqua/Eau, Blue 1, Yellow 5

PACKAGE LABEL

Place Holder Text